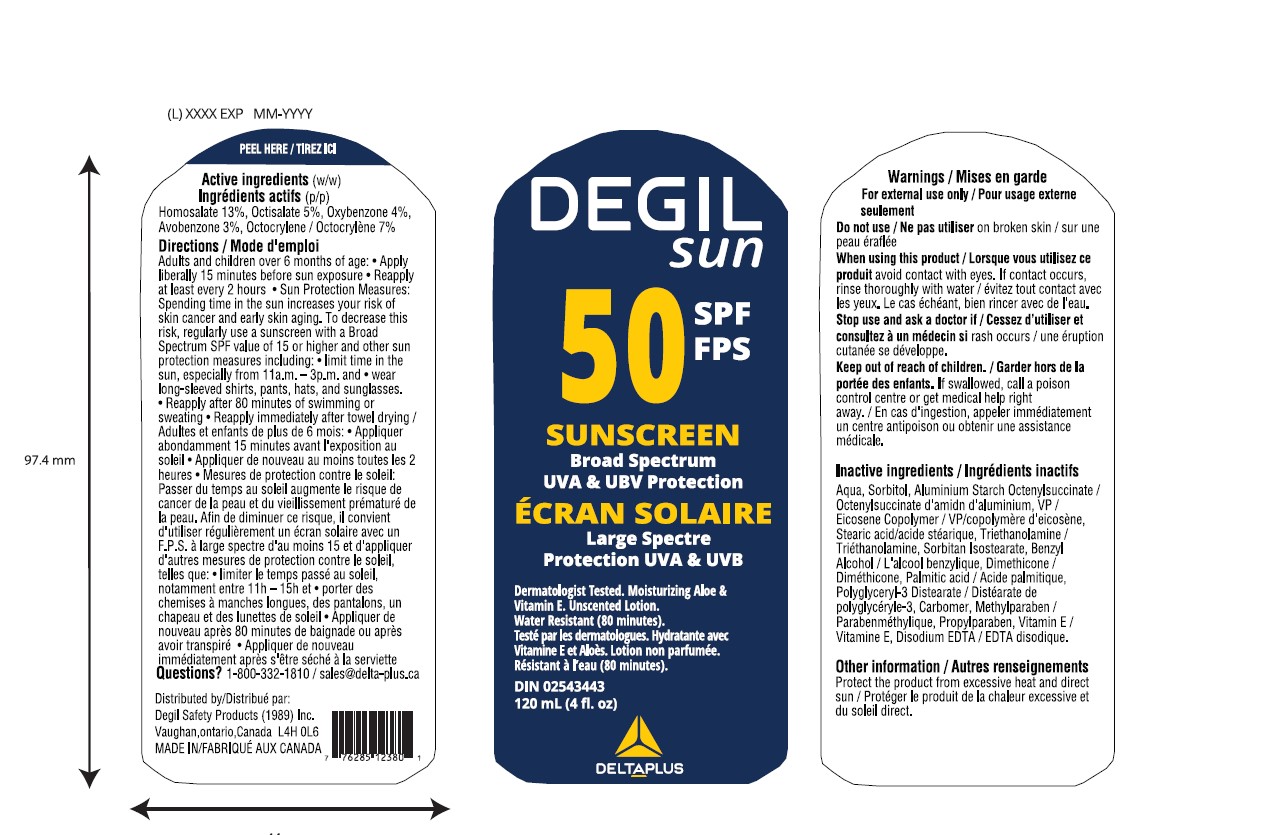 DRUG LABEL: Degil Sun SPF 50 Sunscreen
NDC: 58331-075 | Form: LOTION
Manufacturer: Degil Safety Products (1989) Inc
Category: otc | Type: HUMAN OTC DRUG LABEL
Date: 20240405

ACTIVE INGREDIENTS: OCTISALATE 5 g/100 mL; AVOBENZONE 3 g/100 mL; OXYBENZONE 4 g/100 mL; OCTOCRYLENE 7 g/100 mL; HOMOSALATE 13 g/100 mL
INACTIVE INGREDIENTS: METHYLPARABEN; .ALPHA.-TOCOPHEROL; ALUMINUM STARCH OCTENYLSUCCINATE; SORBITAN ISOSTEARATE; DIMETHICONE; PALMITIC ACID; PROPYLPARABEN; POLYGLYCERYL-3 DISTEARATE; CARBOMER HOMOPOLYMER, UNSPECIFIED TYPE; SORBITOL; VINYLPYRROLIDONE/EICOSENE COPOLYMER; BENZYL ALCOHOL; STEARIC ACID; EDETATE DISODIUM; WATER; TROLAMINE

Degil Sun SPF 50 Sunscreen

ACTIVE INGREDIENT

Homosalate 13%

Octisalate 5%

Oxybenzone 4%

Avobenzone 3%

Octocrylene 7%

PURPOSE

Sunscreen

INDICATIONS AND USAGE

Sun Protection Factor 50 • SPF 50 • Helps prevent sunburn • Sunburn protectant

• Helps protect from sunburn • If used as directed with other sun protection measures [see Directions (for Use)], decreases the risk of skin cancer and early skin aging caused by the sun • Water Resistant (80 minutes)

WARNINGS

For external use only

Do not use on broken skin

When using this product avoid contact with eyes. If contact occurs, rinse thoroughly with water

Stop use and ask a doctor if rash occurs

If swallowed, call a poison control centre or get medical help right away.

Keep out of reach of children

INSTRUCTIONS FOR USE

Adults and children over 6 months of age • Apply liberally/generously (and evenly) 15 minutes before sun exposure • Reapply at least every 2 hours • Sun Protection Measures: Spending time in the sun increases your risk of skin cancer and early skin aging. To decrease this risk, regularly use a sunscreen with a Broad Spectrum SPF value of 15 or higher and other sun protection measures including: ▪ limit time in the sun, especially from 11 a.m. – 3 p.m.; and ▪ wear long-sleeved shirts, pants, hats and sunglasses • Reapply after 80 minutes of swimming or sweating • Reapply immediately after towel drying

INACTIVE INGREDIENT

Aqua, Sorbitol, Aluminium Starch Octenylsuccinate , VP / Eicosene Copolymer, Stearic acid, Triethanolamine, Sorbitan Isostearate, Benzyl Alcohol, Dimethicone, Palmitic acid, Polyglyceryl-3 Distearate, Carbomer, Methylparaben, Propylparaben, Vitamin E, Disodium EDTA

Other information

Protect the product from excessive heat and direct sun

Questions? 1-800-332-1810 / sales@delta-plus.ca

PACKAGE LABEL

DEGIL Sun 50 SPF FPS

SUNSCREEN

Broad Spectrum
UVA & UBV Protection

Protection UVA & UVB

Dermatologist Tested. Moisturizing Aloe &
Vitamin E. Unscented Lotion.
Water Resistant (80 minutes).

DIN 02543443

120 mL(4 fl.oz.)/750 mL(25 fl.oz.)

Distributed by
Degil Safety Products (1989) Inc.
Vaughan,ontario,Canada L4H 0L6
MADE IN CANADA

DOSAGE AND ADMINISTRATION

Lotion

Topical